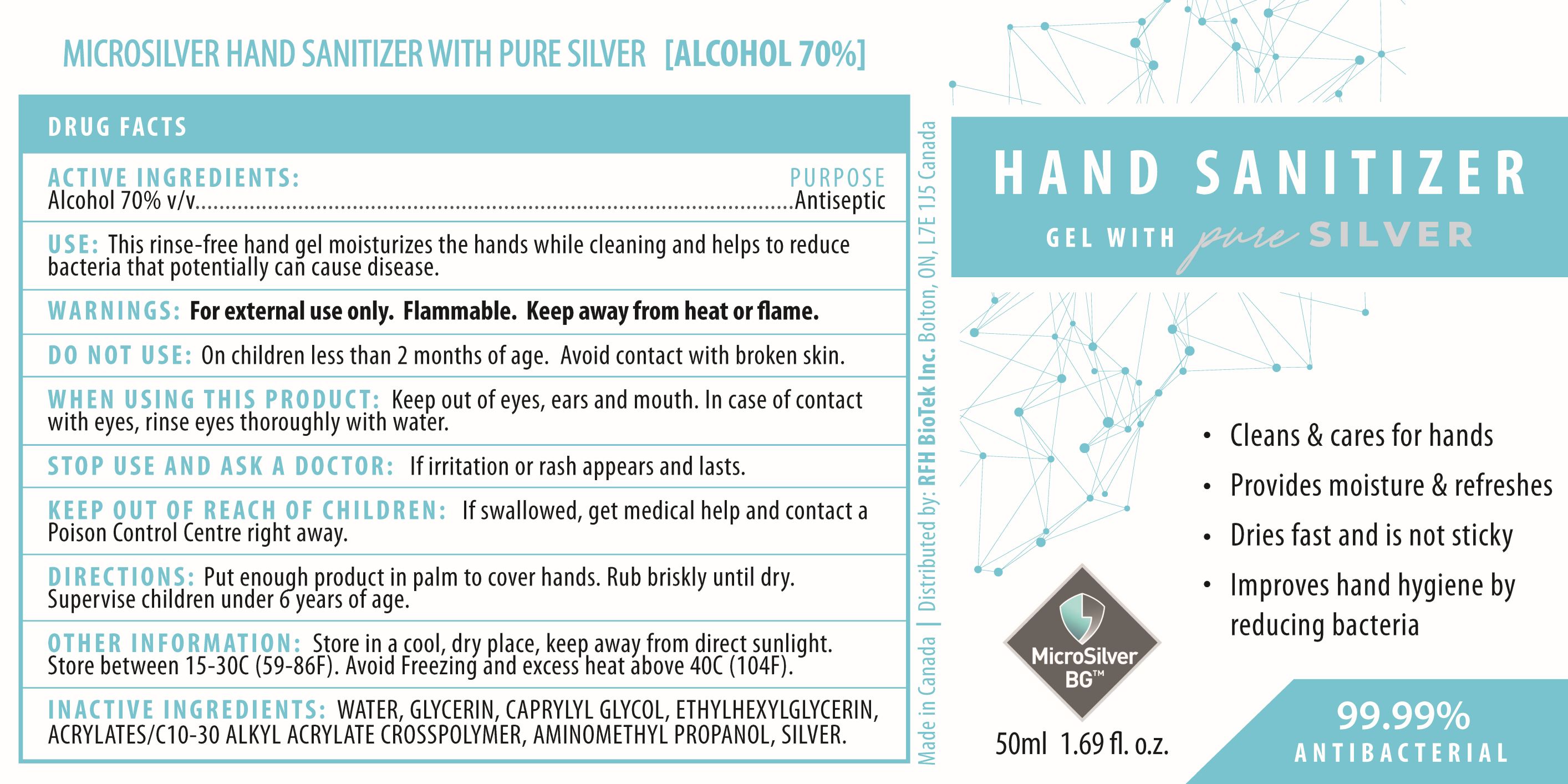 DRUG LABEL: Hand Sanitizer gel
NDC: 78994-070 | Form: GEL
Manufacturer: RFH BioTek Inc.
Category: otc | Type: HUMAN OTC DRUG LABEL
Date: 20220720

ACTIVE INGREDIENTS: ALCOHOL 70 mL/100 mL
INACTIVE INGREDIENTS: WATER; GLYCERIN; CAPRYLYL GLYCOL; AMINOMETHYLPROPANOL; SILVER; ETHYLHEXYLGLYCERIN; CARBOMER INTERPOLYMER TYPE A (ALLYL SUCROSE CROSSLINKED)

HAND SANITIZER GEL WITH pure SILVER - Alcohol gel

ACTIVE INGREDIENTS

Alcohol 70% v/v

PURPOSE

Antiseptic

USE

This rinse-free hand gel moisturizes the hands while cleaning and helps to reduce bacteria that potentially can cause disease.

WARNINGS

For external use only. Flammable. Keep away from heat or flame.

DO NOT USE

On children less than 2 months of age. Avoid contact with broken skin.

WHEN USING THIS PRODUCTS

Keep out of eyes, ears and mouth. In case of contact with eyes, rinse eyes thoroughly with water.

STOP USE AND ASK A DOCTOR

If irritation or rash appears and lasts.

KEEP OUT OF REACH OF CHILDREN

If swallowed, get medical help and contact a Poison Control Centre right away.

DIRECTIONS

Put enough product in palm to cover hands. Rub briskly until dry. Supervise children under 6 years of age.

OTHER INFORMATION

Store in a cool, dry place, keep away from direct sunlight. Store between 15-30C (59-86F). Avoid Freezing and excess heat above 40C (104F).

INACTIVE INGREDIENTS

WATER, GLYCERIN, CAPRYLYL GLYCOL, ETHYLHEXYLGLYCERIN, ACRYLATES/C10-30 ALKYL ACRYLATE CROSSPOLYMER, AMINOMETHYL PROPANOL, SILVER.

PACKAGE LABEL

HAND SANITIZER

GEL WITH pure SILVER

- Cleans & care for hands
- Provides moisture & refreshes
- Dries fast and is not sticky
- Improves hand hygiene by reducing bacteriria

MicroSilver

BG™

99.99%

ANTIBACTERIAL